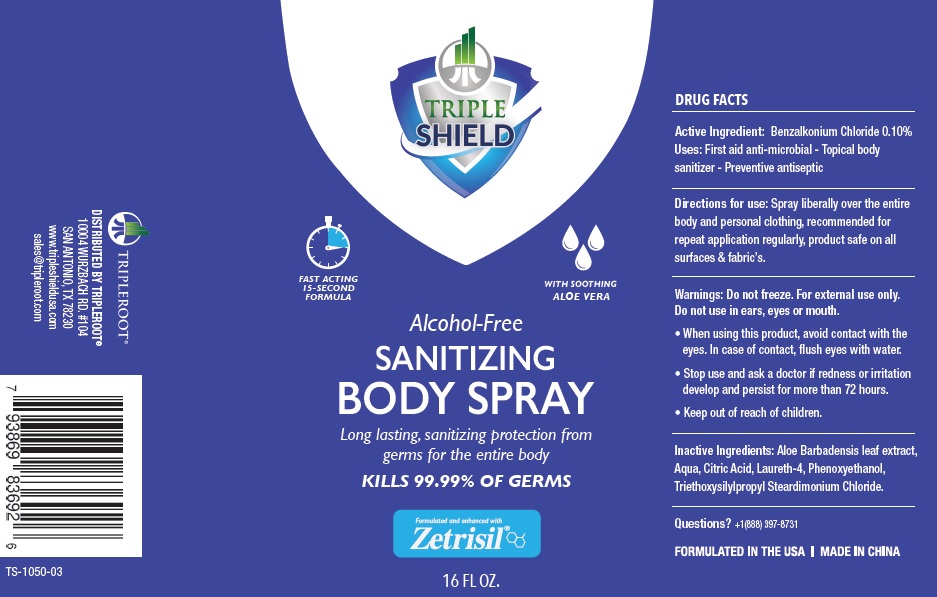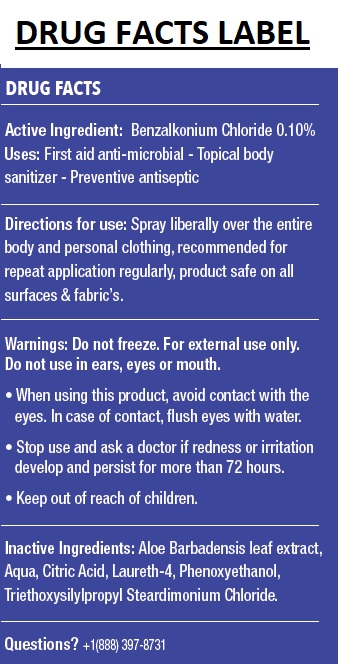 DRUG LABEL: TRIPLE SHIELD
NDC: 71884-034 | Form: SPRAY
Manufacturer: Enviro Specialty Chemicals Inc
Category: otc | Type: HUMAN OTC DRUG LABEL
Date: 20241231

ACTIVE INGREDIENTS: BENZALKONIUM CHLORIDE 0.10 g/100 mL
INACTIVE INGREDIENTS: ALOE VERA LEAF; WATER; CITRIC ACID MONOHYDRATE; LAURETH-4; PHENOXYETHANOL; TRIETHOXYSILYLPROPYL STEARDIMONIUM CHLORIDE

TRIPLE SHIELD Alcohol-Free SANITIZING BODY SPRAY

Active Ingredient: Benzalkonium Chloride 0.10%

Purpose: Antiseptic

INDICATIONS AND USAGE

Uses: First aid anti-microbial - Topical body sanitizer - Preventive antiseptic

DOSAGE AND ADMINISTRATION

Directions for use: Spray liberally over the entire body and personal clothing, recommended for repeat application regularly, product safe on all

surfaces & fabric’s.

Warnings: Do not freeze. For external use only.

Do not use in ears, eyes or mouth.

• When using this product, avoid contact with the eyes. In case of contact, flush eyes with water.

• Stop use and ask a doctor if redness or irritation develop and persist for more than 72 hours.

• Keep out of reach of children.

INACTIVE INGREDIENT

Inactive Ingredients: Aloe Barbadensis leaf extract, Aqua, Citric Acid, Laureth-4, Phenoxyethanol, Triethoxysilylpropyl Steardimonium Chloride.

Questions? +1(888) 397-8731

FAST ACTING

15-SECOND FORMULA

WITH SOOTHING

ALOE VERA

Long lasting, sanitizing protection from germs for the entire body

KILLS 99.99% OF GERMS

Formulated and enhanced with

Zetrisil®

DISTRIBUTED BY TRIPLEROOT®

10004 WURZBACH RD. #104

SAN ANTONIO, TX 78230

www.tripleshieldusa.com

sales@tripleroot.com

FORMULATED IN THE USA | MADE IN CHINA